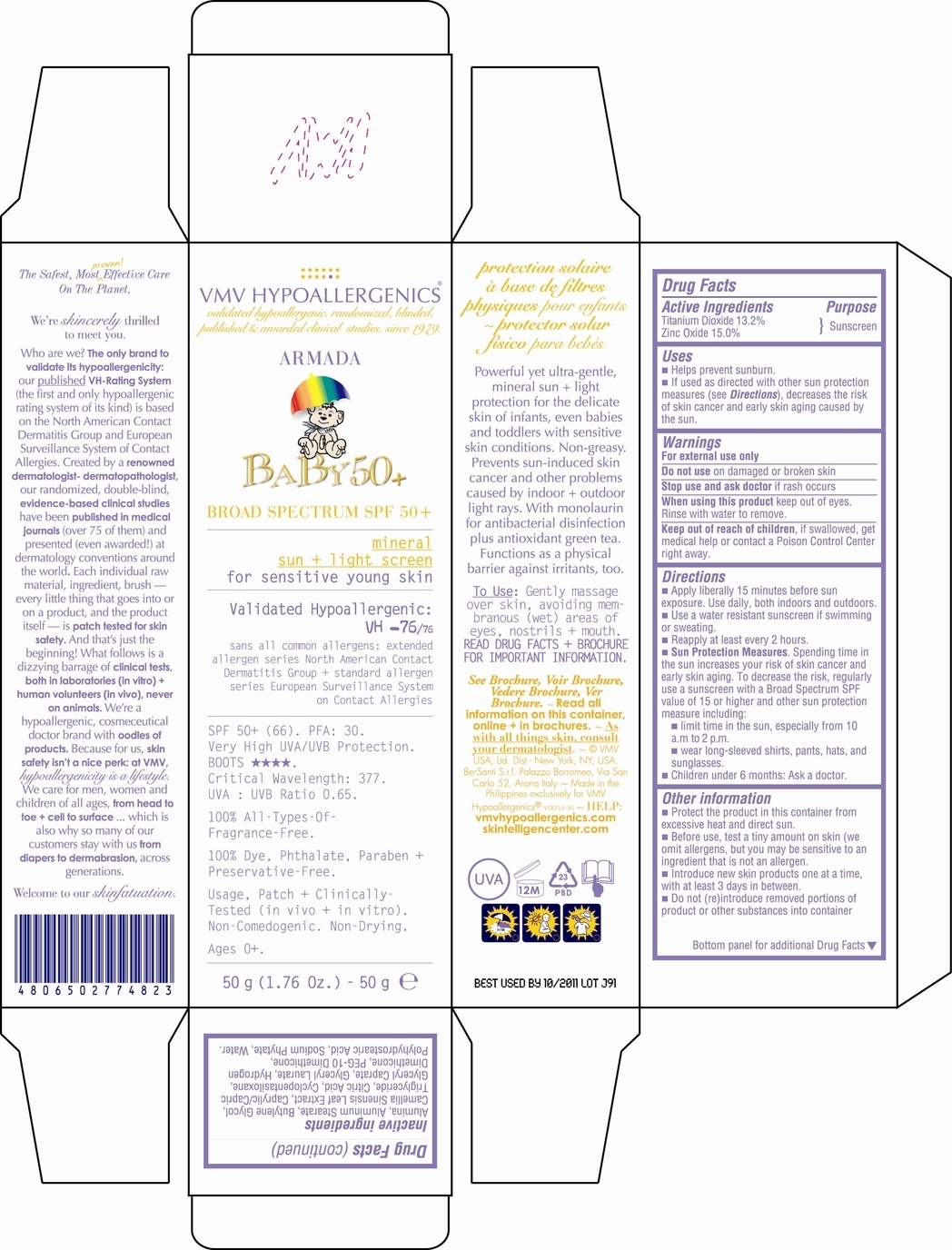 DRUG LABEL: VMV HYPOALLERGENICS ARMADA BABY 50
NDC: 69774-103 | Form: CREAM
Manufacturer: SKIN SCIENCES LABORATORY INC.
Category: otc | Type: HUMAN OTC DRUG LABEL
Date: 20150915

ACTIVE INGREDIENTS: TITANIUM DIOXIDE 13.2 g/50 g; ZINC OXIDE 15 g/50 g
INACTIVE INGREDIENTS: WATER

Uses

- Helps prevent sunburn.

- If used as directed with other sun protection measures (see Directions) , decrease the risk of skin cancer and aerly skin aging caused by the sun.

Warnings

For External use only.

Do not use on damaged or broken skin.

Stop use and ask doctor if rash occurs.

When using this product keep out of eyes.

Rinse with water to remove.

Keep out of reach of children, if swallowed, get medical help or contact a Poison Control Center right away.

Directions

- Apply liberally 15 minutes before sun exposure.

- Use a water resistant sunscreen if swimming or sweating.

- Re-apply atleast evry 2 hours.

- Sun protection measures. Spending time in the sun increases your risk of skin cancer and early skin aging. To decrease the risk, regularly use a sunscreen with a Broad Spectrum SPF value of 15 or higher and other sun protection measure including:

- Limit time in the sun, especially from 10am to 12pm.

- Wear a long-sleeved shirts, pants, hats and sunglasses.

- Children under 6months: Ask a Doctor.

Other Informations

- Protect the product in this container from excessive heat and direct sun.

- Before use, test a tiny amount on skin (we omit allergen, but you may be sensitive to an ingredient that is not an allergen).

- Introduce new skin products one at a tim, with atleast 3 days in between.

- Do not (re)introduce removed portions of products or other substances into container.

Inactive Ingredients

Alumina, Aluminum Stearate, Butylene Glycol, Camellia Sinensis Leaf Extract, Caprylic/Capric Triglyceride, Citric Acid, Cyclopentanosiloxane, Glyceryl Caprate, Glyceryl Laurate, Hydrogen Dimethicone, PEG-10, Dimethicone, Polyhydrostearic Acid, Sodium Phytate, Water.

Active Ingredient

Titanium Dioxide

Zinc Oxide

Active Ingredient

Titanium Dioxide - 13.2%

Zinc Oxide - 15.0%

Principal Display Panel

VMV HYPOALLERGENICS

validated hypoallergenics. randomized, blinded, published & awarded clinical studies, since 1979.

ARMADA

BABY 50+

BROAD SPECTRUM SPF 50+

mineral

sun + light screen

for sensitive young skin

Validated Hypoallergenic:

VH -76/76

sans all common allergens:

extended allergen series

North American Contact Dermatitis

Group + Standard allergen series

European Survellance System of

Contact Allergies

SPF: 50+ (66). PFA: 30.

Very High UVA/UVB Protection.

Boots (5stars).

Critical Wavelenght: 377.

UVA:UVB Ratio = 0.65.

100% All-Types-Of-Frangrance-Free.

100% Dye-Phthalate-PABA-

Paraben + Preservative-Free.

Usage, Patch +Clinically-

Tested (in vivo + in vitro).

Non-Comedogenic. Non-Drying.

Ages 0+

50g (1.76 Oz.) - 50g e